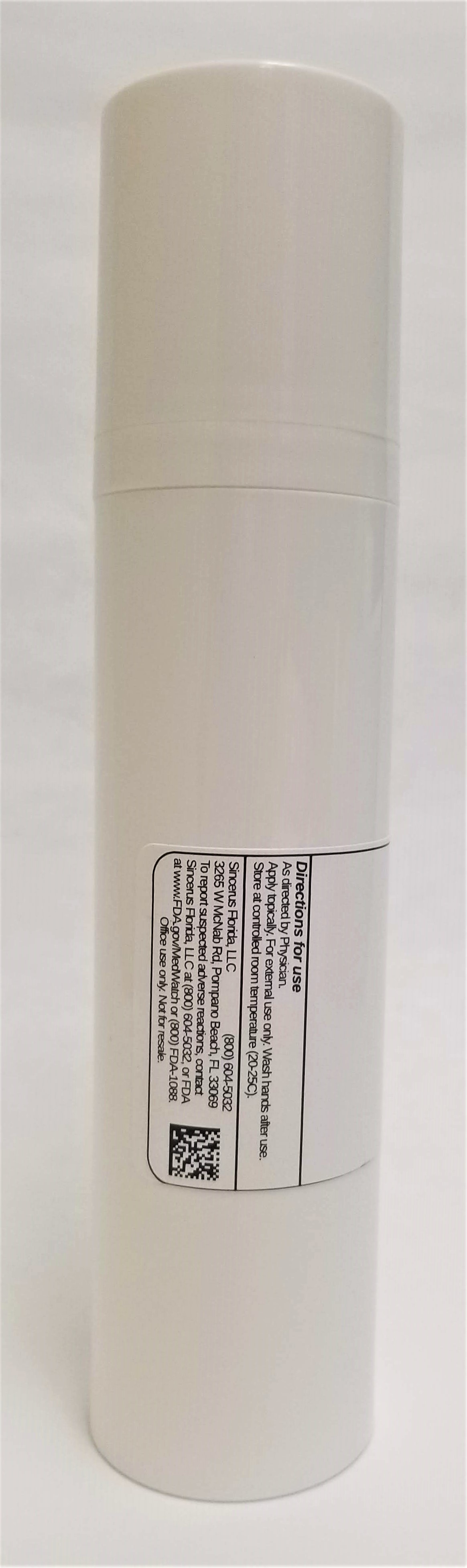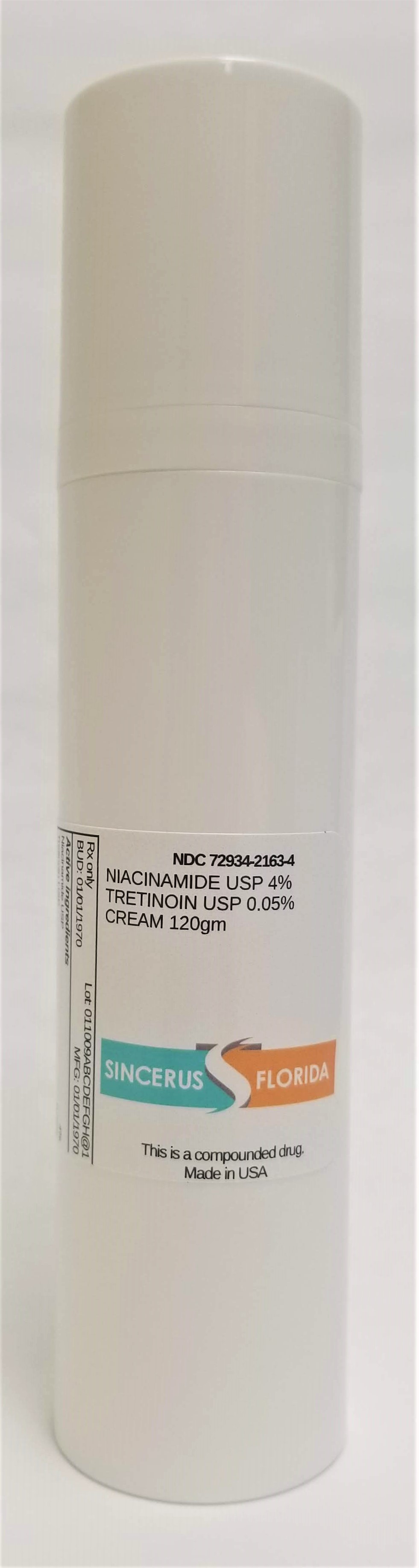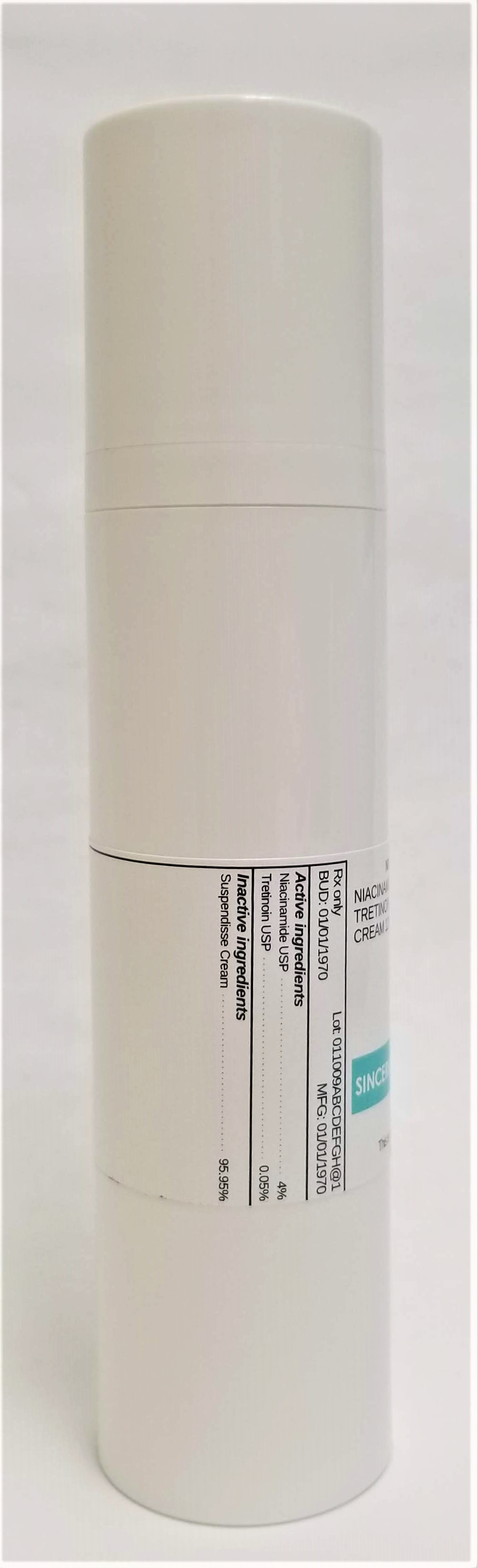 DRUG LABEL: NIACINAMIDE 4% / TRETINOIN 0.05%
NDC: 72934-2163 | Form: CREAM
Manufacturer: Sincerus Florida, LLC
Category: prescription | Type: HUMAN PRESCRIPTION DRUG LABEL
Date: 20190506

ACTIVE INGREDIENTS: TRETINOIN 0.05 g/100 g; NIACINAMIDE 4 g/100 g

NIACINAMIDE 4% / TRETINOIN 0.05%